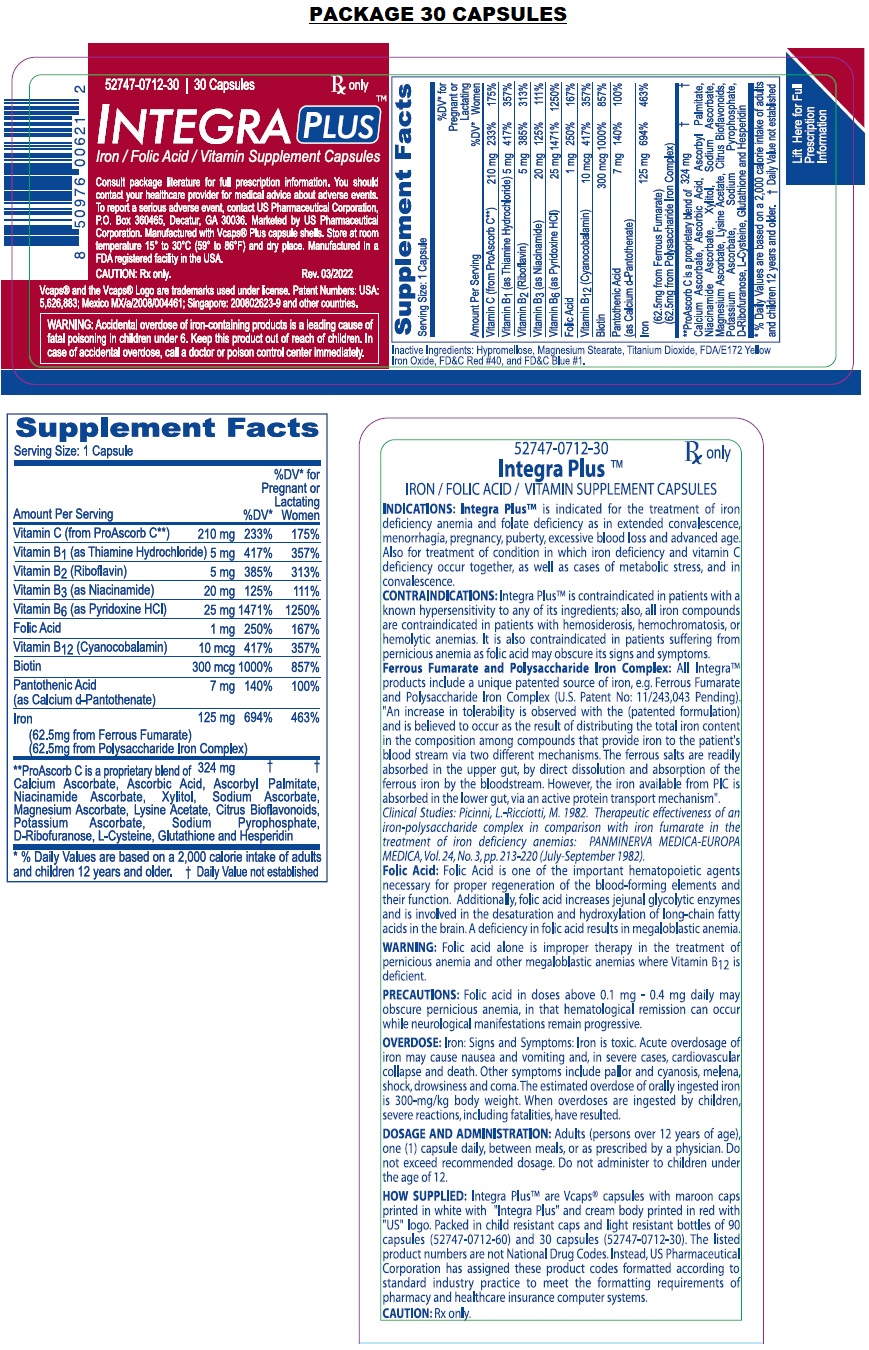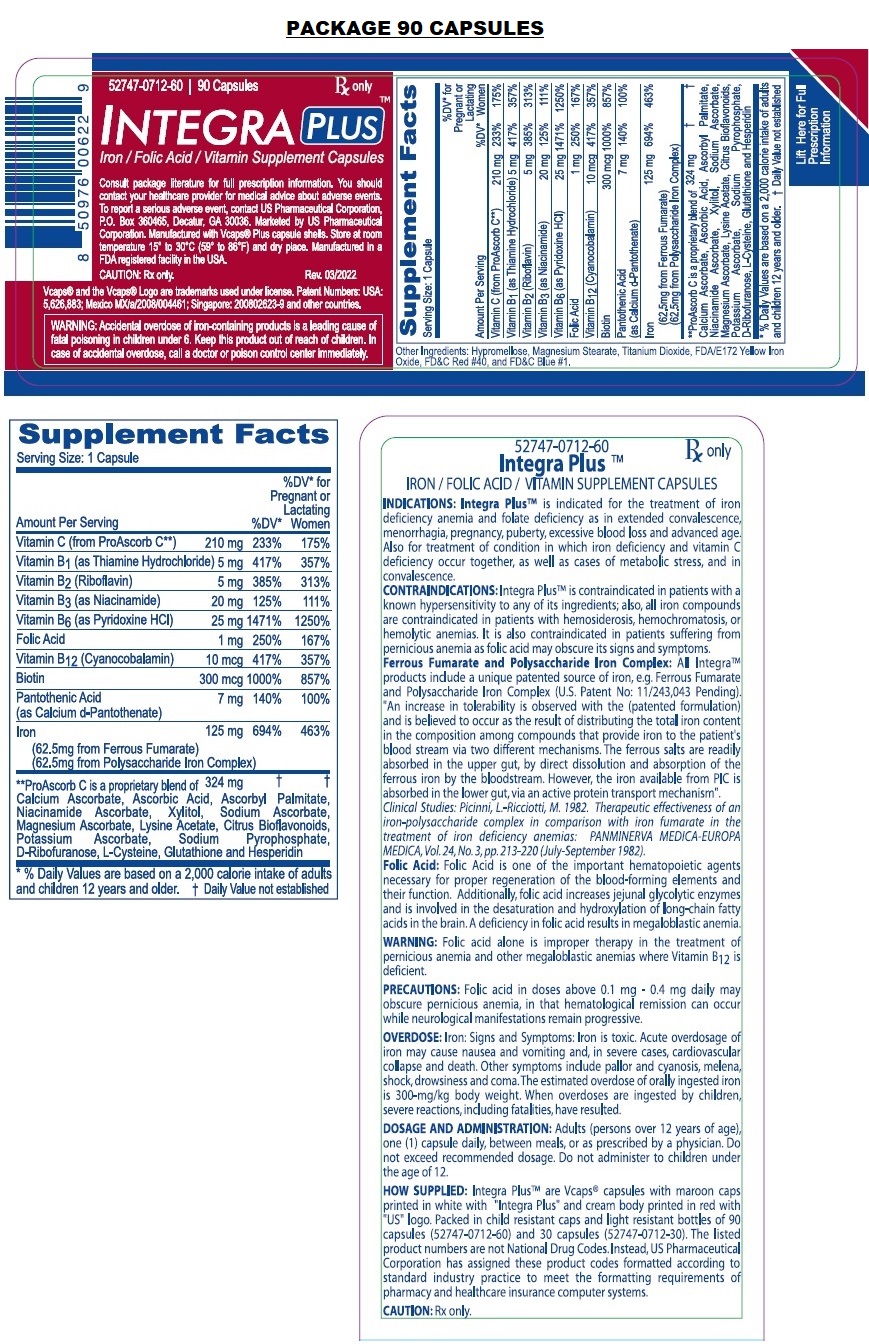 DRUG LABEL: Integra Plus 
NDC: 52747-712 | Form: CAPSULE
Manufacturer: U.S. Pharmaceutical Corporation
Category: prescription | Type: HUMAN PRESCRIPTION DRUG LABEL
Date: 20240403

ACTIVE INGREDIENTS: FERROUS FUMARATE 62.5 mg/1 1; FERROUS ASPARTO GLYCINATE 62.5 mg/1 1; FOLIC ACID 1 mg/1 1; ASCORBIC ACID 210 mg/1 1; NIACIN 20 mg/1 1; THIAMINE MONONITRATE 5 mg/1 1; RIBOFLAVIN 5 mg/1 1; CALCIUM PANTOTHENATE 5 mg/1 1; PYRIDOXINE HYDROCHLORIDE 25 mg/1 1; BIOTIN 300 ug/1 1
INACTIVE INGREDIENTS: HYPROMELLOSE, UNSPECIFIED; MAGNESIUM STEARATE; TITANIUM DIOXIDE; FERRIC OXIDE YELLOW; FD&C RED NO. 40; FD&C BLUE NO. 1

see all prescribing information for Integra Plus

DESCRIPTION

DESCRIPTION: Each capsule contains: Ferrous Fumarate (anhydrous) ......191.1 mg Polysaccharide Iron Complex... 135.9 mg (Equivalent to about 125 mg of elemental iron) Vitamin C (from ProAscorb C‡)....210 mg Folic Acid .....1 mg Thiamine Mononitrate (B1)...5 mg Riboflavin (B2)....5 mg Niacin (B3) . 20 mg d-Calcium Pantothenate (B5)..7 mg Pyridoxine HCl (B6) ...25 mg Biotin (B7)......300 mcg Cyanocobalamin (B12) .. 10 mcg

CLINICAL PHARMACOLOGY

CLINICAL PHARMACOLOGY: Integra PlusTM is unique in that it utilizes two (2) different forms of iron, i.e., Ferrous Fumarate and Polysaccharide Iron Complex (as cell-contracted akaganèite), making available a total of 125 mg of elemental iron per capsule as follows:
Ferrous Fumarate (anhydrous) 191.1 mg Polysaccharide iron complex (PIC) 135.9 mg
Subclinical B-Group vitamin deficiencies have greatly increased in recent years, due to changes in dietetic habits, increase in the use of sugar, and the excessive milling of flour and cereals. With thiamine deficiencies in a healthy populous, it is self-evident that the unwell person is particularly prone to thiamine avitaminosis. This is true of the anemic individual with his/her poor appetite and disturbed digestive functions. Folic acid is best known for its role in megaloblastic anemias. Zinc has been recognized in the nutrition of animals and humans, even though the evidence for an uncomplicated zinc deficiency in humans is limited.
Ferrous Fumarate: Provides about 62.5 mg of elemental iron per dose. Ferrous Fumarate is an anhydrous salt of a combination of ferrous iron and fumaric acid, containing 33% of iron per weight. The acute toxicity in experimental animals is low and Ferrous Fumarate is well tolerated clinically. As a ferrous salt, it is more efficiently absorbed in the duodenum. Ferrous Fumarate contrasts very favorably with the availability of the 20% of elemental iron of ferrous sulfate, and the 13% of elemental iron of ferrous gluconate.
Polysaccharide Iron Complex: Provides about 62.5 mg elemental iron, as a cell-contracted akaganèite. It is a product of ferric iron complexed to a low molecular weight polysaccharide. This polysaccharide is produced by the extensive hydrolysis of starch and is a dark brown powder that dissolves in water to form a very dark brown solution, which is virtually odorless and tasteless.
Folic Acid: Folic Acid is one of the important hematopoetic agents necessary for proper regeneration of the blood-forming elements and their function. Folic acid is a precursor of a large family of compounds which serve as coenzymes in carbon transfer reactions. These reactions are required for the synthesis of purine and pyrimidine bases, inter-conversion of glycine and serine, biosynthesis of methionine methyl groups and degradation of histidine. Additionally, folic acid increases jejunal glycolytic enzymes and is involved in the desaturation and hydroxylation of long-chain fatty acids in the brain. A deficiency in folic acid results in megaloblastic anemia.
All IntegraTM products include a unique patented source of iron, e.g. Ferrous Fumarate and Polysaccharide Iron Complex (U.S. Patent No: 11/243,043 Pending). "An increase in tolerability is observed with the (patented formulation) and is believed to occur as the result of distributing the total iron content in the composition among compounds that provide iron to the patient's blood stream via two different mechanisms. The ferrous salts are readily absorbed in the upper gut, by direct dissolution and absorption of the ferrous iron by the bloodstream. However, the iron available from PIC is absorbed in the lower gut, via an active protein transport mechanism".

CLINICAL STUDIES

Clinical Studies: Because Ferrous Fumarate is an organic complex, it contains no free ions, either ferric or ferrous. Polysaccharide Iron Complex is clinically non-toxic. Prior studies in rats demonstrated that Polysaccharide Iron Complex (PIC), administered as a single oral dose to Sprague Dawley rats did not produce evidence of toxicity at a dosage level of 5000 mg Iron/kg: (An Acute Oral Toxicity Study in Rats with Polysaccharide-Iron Complex. T.N.Merriman, M. Aikman and R.E. Rush, Springborn Laboratories. Inc. Spencerville, Ohio Study No. 3340.1 March - April 1994). Other clinical studies had demonstrated that Polysaccharide Iron gives a good hematopoietic response with an almost complete absence of the side effects usually associated with oral iron therapy. Picinni and Ricciotti suggested in 1982, that "the therapeutic effectiveness of Polysaccharide Iron Complex when compared with iron fumarate in the treatment of iron deficiency anemia, appears to be as active as the iron fumarate and as well tolerated, however, it exerted a greater influence on the level of hemoglobin and on the number of red cells..." and that, "it has been exceptionally well tolerated by all patients" (Picinni, L.-Ricciotti, M. 1982. Therapeutic effectiveness of an iron-polysaccharide complex in comparison with iron fumarate in the treatment of iron deficiency anemias): PANMINERVA MEDICA-EUROPA MEDICA, Vol. 24, No. 3, pp. 213-220 (July-September 1982).
As mentioned above, the patented source of iron used in Integra PlusTM (Ferrous Fumarate and Polysaccharide Iron Complex) provides a high level of elemental iron with a low incidence of gastric distress.
CONCLUSION: Based on the results of this study, the oral combination of Ferrous Fumarate and Polysaccharide Iron Complex was better tolerated and safer than the oral administration of Ferrous Fumarate alone. The conclusion of this research stated, that the addition of PIC to Ferrous Fumarate surprisingly allows the same concentration of Ferrous Fumarate to be better tolerated than the Ferrous Fumarate alone.

CONTRAINDICATIONS

CONTRAINDICATIONS: Integra PlusTM is contraindicated in patients with a known hypersensitivity to any of its ingredients; also, all iron compounds are contraindicated in patients with hemosiderosis, hemochromatosis, or hemolytic anemias. Pernicious anemia is a contraindication, as folic acid may obscure its signs and symptoms.

WARNINGS AND PRECAUTIONS

WARNING: Accidental overdose of iron-containing products is a leading cause of fatal poisoning in children under 6. Keep this product out of reach of children. In case of accidental overdose, call a doctor or poison control center immediately.
WARNING: Folic acid alone is improper therapy in the treatment of pernicious anemia and other megaloblastic anemias where Vitamin B12 is deficient.
PRECAUTIONS: General: Folic acid in doses above 0.1 mg - 0.4 mg daily may obscure pernicious anemia, in that hematological remission can occur while neurological manifestations remain progressive. Pediatric Use: Safety and effectiveness of this product have not been established in pediatric patients. Geriatric Use: No clinical studies have been performed in patients age 65 and over to determine whether older persons respond differently from younger persons. Dosage should always begin at the low end of the dosage scale and should consider that elderly persons may have decreased hepatic, renal, or cardiac function and or concomitant diseases.

ADVERSE REACTIONS

Adverse Reactions: Folic Acid: Allergic sensitizations have been reported following both oral and parenteral administration of folic acid. Ferrous Fumarate: Gastrointestinal disturbances (anorexia, nausea, diarrhea, constipation) occur occasionally, but are usually mild and may subside with continuation of therapy. Although the absorption of iron is best when taken between meals, giving Integra PlusTM after meals may control occasional G.I. disturbances. Integra PlusTM is best absorbed when taken at bedtime.

OVERDOSAGE

OVERDOSE: Iron: Signs and Symptoms: Iron is toxic. Acute overdosage of iron may cause nausea and vomiting and, in severe cases, cardiovascular collapse and death. Other symptoms include pallor and cyanosis, melena, shock, drowsiness and coma. The estimated overdose of orally ingested iron is 300-mg/kg body weight. When overdoses are ingested by children, severe reactions, including fatalities, have resulted. Integra PlusTM should be stored beyond the reach of children to prevent against accidental iron poisoning. Keep this and all other drugs out of the reach of children.
Treatment: For specific therapy, exchange transfusion and chelating agents should be used. For general management, perform gastric lavage with sodium bicarbonate solution or milk. Administer intravenous fluids and electrolytes and use oxygen.

DOSAGE AND ADMINISTRATION: Adults (persons over 12 years of age), One (1) capsule daily, between meals, or as prescribed by a physician. Do not exceed recommended dosage. Do not administer to children under the age of 12.

PEDIATRIC USE

Pediatric Use: Safety and effectiveness of this product have not been established in pediatric patients.

GERIATRIC USE

Enter section text here

HOW SUPPLIED

HOW SUPPLIED: Integra PlusTM are Vcaps® capsules with maroon caps printed in white with "Integra Plus" and cream body printed in red with "US" logo. Packed in child resistant caps and light resistant bottles of 90 capsules (52747-0712-60) and 30 capsules (52747-0712-30). The listed product numbers are not National Drug Codes. Instead, US Pharmaceutical Corporation has assigned these product codes formatted according to standard industry practice to meet the formatting requirements of pharmacy and healthcare insurance computer systems.

CAUTION: Rx only.